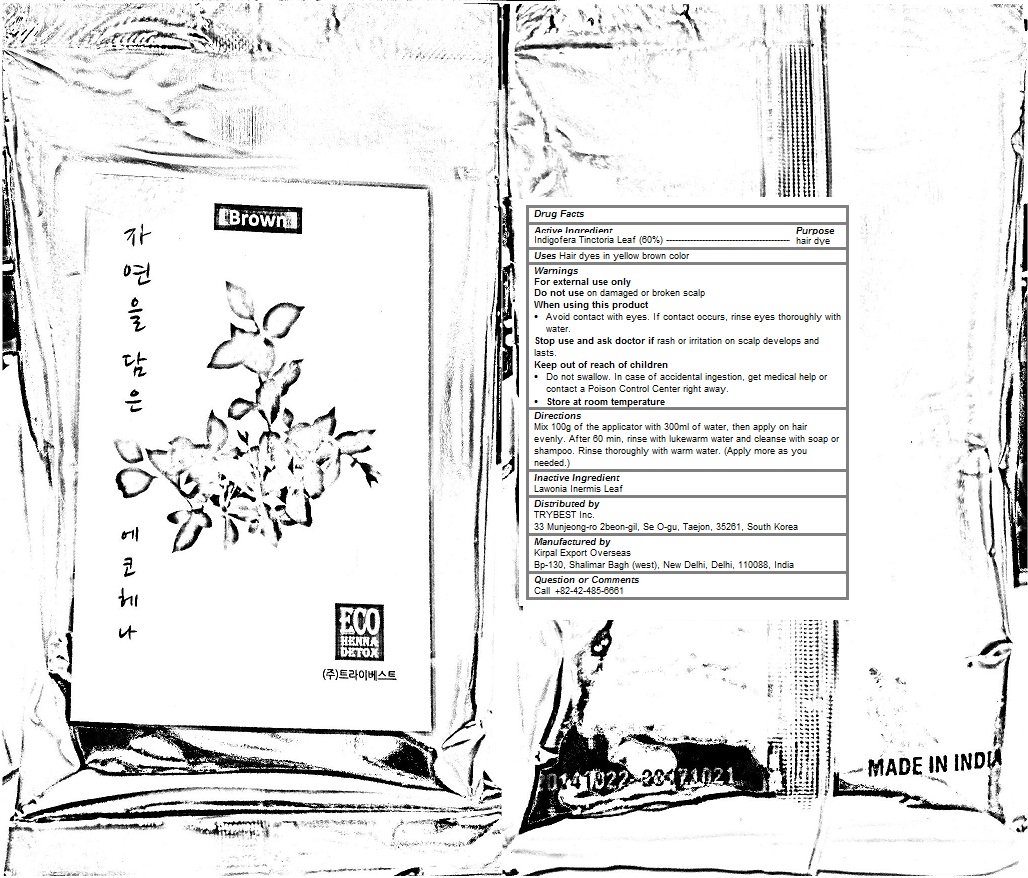 DRUG LABEL: EDP BROWN
NDC: 70434-103 | Form: POWDER
Manufacturer: EDP Inc.
Category: otc | Type: HUMAN OTC DRUG LABEL
Date: 20190115

ACTIVE INGREDIENTS: INDIGOFERA TINCTORIA LEAF 0.6 1/100 g
INACTIVE INGREDIENTS: LAWSONIA INERMIS LEAF 0.4 1/100 g

EDP BROWN